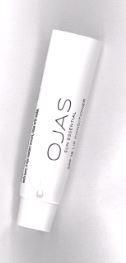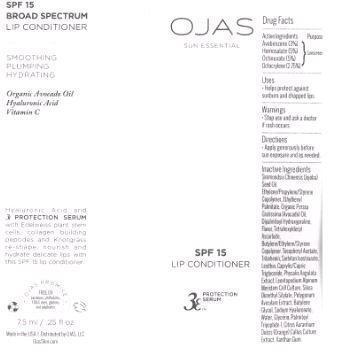 DRUG LABEL: SPF 15 Lip Conditioner
NDC: 70867-102 | Form: CREAM
Manufacturer: OJAS, LLC
Category: otc | Type: HUMAN OTC DRUG LABEL
Date: 20160726

ACTIVE INGREDIENTS: AVOBENZONE 30.0 mg/1 mL; HOMOSALATE 50.0 mg/1 mL; OCTINOXATE 50.0 mg/1 mL; OCTOCRYLENE 27.5 mg/1 mL
INACTIVE INGREDIENTS: JOJOBA OIL; STYRENE; ETHYLHEXYL PALMITATE; AVOCADO OIL    ; DIPALMITOYL HYDROXYPROLINE; TETRAHEXYLDECYL ASCORBATE; 1-BUTENE; ETHYLENE; .ALPHA.-TOCOPHEROL ACETATE; TRIBEHENIN; SORBITAN ISOSTEARATE; EGG PHOSPHOLIPIDS; MEDIUM-CHAIN TRIGLYCERIDES; PHYSALIS ANGULATA; LEONTOPODIUM NIVALE SUBSP. ALPINUM FLOWER; SILICA DIMETHYL SILYLATE; POLYGONUM AVICULARE TOP; BUTYLENE GLYCOL; HYALURONATE SODIUM; WATER; GLYCERIN; PALMITOYL TRIPEPTIDE-1; CITRUS SINENSIS FLOWER; XANTHAN GUM

Active Ingredients:

Avobenzone - 3%

Homosalate - 5%

Octinoxate - 5%

Octocrylene - 2.75%

Purpose: Sunscreen

Uses:

- Helps protect against sunburn and chapped lips.

Warnings:

Stop use and ask a doctor if rash occurs.

Directions:

- Apply generously before sun exposure and as needed.

Inactive Ingredients:

Simmondsia Chinensis (Jojoba) Seed Oil, Ethylene/Propylene/Styrene Copolymer, Ethylhexyl Palmitate, Organic Persea Gratissima (Avocado) Oil, Dipalmitoyl Hydroxyproline, Flavor, Tetrahexyldecyl Ascorbate, Butylene/Ethylene/Styrene Copolymer, Tocopheryl Acetate, Tribehenin, Sorbitan Isostearate, Lecithin, Caprylic/Capric Triglyceride, Physalis Angulata, Extract, Leontopodium Alpinum Meristem Cell Culture, Silica Dimethyl Silylate, Polygonum Aviculare Extract, Butylene Glycol, Sodium Hyaluronate, Water, Glycerin, Palmitoyl Tripeptide-1, Citrus Aurantium Dulcis (Orange) Callus Culture Extract, Xanthan Gum.

PACKAGE LABEL

Made In USA

Distributed By OJAS, LLC

OjasSkin.Com